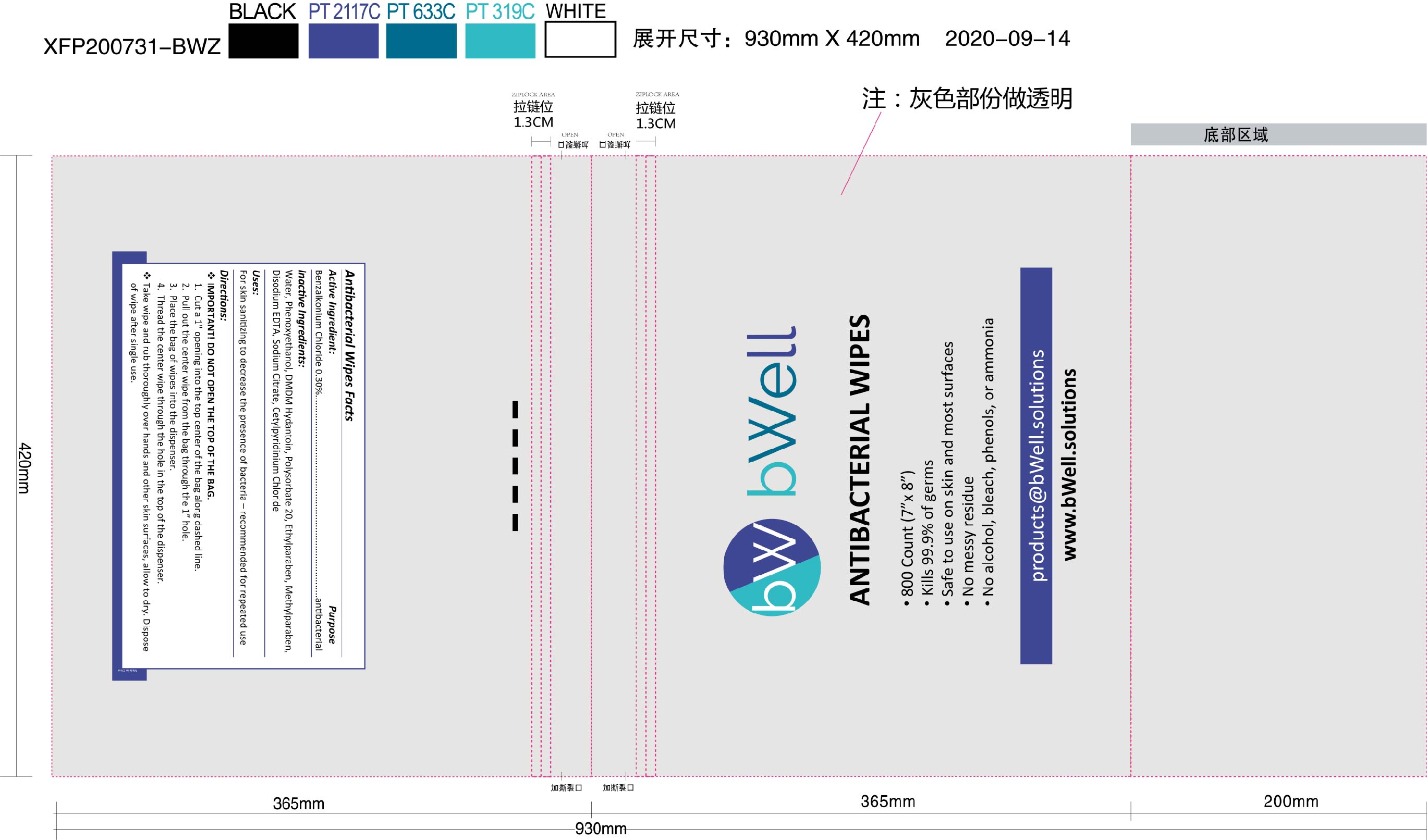 DRUG LABEL: Antibacterial Wipes
NDC: 78494-002 | Form: CLOTH
Manufacturer: Fitguard
Category: otc | Type: HUMAN OTC DRUG LABEL
Date: 20220127

ACTIVE INGREDIENTS: BENZALKONIUM CHLORIDE 0.3 mg/1 1
INACTIVE INGREDIENTS: CETYLPYRIDINIUM CHLORIDE 0.01 mg/1 1; PHENOXYETHANOL 0.45 mg/1 1; DMDM HYDANTOIN 0.275 mg/1 1; ETHYLPARABEN 0.09 mg/1 1; WATER 98.575 1/1 1; POLYSORBATE 20 0.2 mg/1 1; DISODIUM EDTA-COPPER 0.02 mg/1 1; SODIUM CITRATE 0.02 mg/1 1; METHYLPARABEN 0.06 mg/1 1

B-Well Antibacterial Wipes, 800 Count

Active Ingredient:

Benzalkonium Chloride 0.30%

Purpose

Antibacterial

Inactive Ingredients:

Water, Phenoxyethanol, DMDM Hydantoin, Polysorbate 20, Ethylparaben, Methylparaben, Disodium EDTA, Sodium Citrate, Cetylpyridinium Chloride

Uses:

For skin sanitizing to decrease the presence of bacteria - recommended for repeated use

Warnings:

For external use only.

May irritate eyes.

Keep out of reach of children unless under adult supervision.

Warnings:

Keep out of reach of children unless under adult supervision.

Directions:

Important! Do not open the top of the bag.

1. Cut a 1" opening into the top center of the bag along dashed line.

2. Pull out the center wipe from the bag through the 1" hole.

3. Place bag of wipes into the dispenser.

4. Thread the center wipe through the hole in the top of the dispenser.

Take wipe and rub thoroughly over hands and other skin surfaces, allow to dry. Dispose of wipe after single use.

Directions:

Take wipe and rub thoroughly over hands and other skin surfaces, allow to dry. Dispose of wipe after single use.